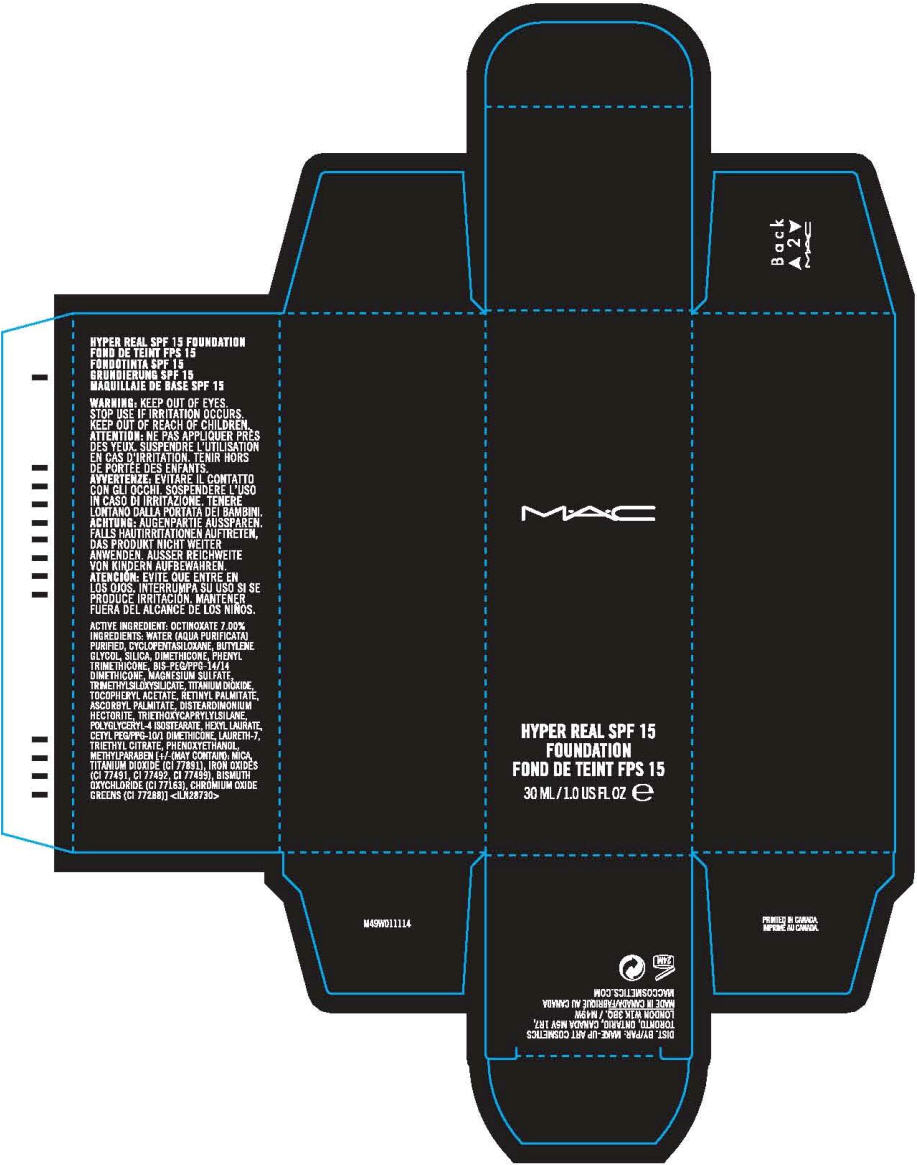 DRUG LABEL: MAC 
NDC: 40046-0056 | Form: LIQUID
Manufacturer: MAKEUP ART COSMETICS
Category: otc | Type: HUMAN OTC DRUG LABEL
Date: 20120502

ACTIVE INGREDIENTS: OCTINOXATE 7 mL/100 mL
INACTIVE INGREDIENTS: WATER; CYCLOMETHICONE 5; BUTYLENE GLYCOL; SILICON DIOXIDE; DIMETHICONE; PHENYL TRIMETHICONE; MAGNESIUM SULFATE; TITANIUM DIOXIDE; .ALPHA.-TOCOPHEROL ACETATE; VITAMIN A PALMITATE; ASCORBYL PALMITATE; TRIETHOXYCAPRYLYLSILANE; POLYGLYCERYL-4 ISOSTEARATE; HEXYL LAURATE; LAURETH-7; TRIETHYL CITRATE; PHENOXYETHANOL; METHYLPARABEN; MICA; FERRIC OXIDE RED; FERRIC OXIDE YELLOW; FERROSOFERRIC OXIDE; BISMUTH OXYCHLORIDE; CHROMIC OXIDE

M•A•C
HYPER REAL SPF 15 FOUNDATION

WARNING

WHEN USING

KEEP OUT OF EYES.

STOP USE IF IRRITATION OCCURS.

KEEP OUT OF REACH OF CHILDREN.

ACTIVE INGREDIENT

OCTINOXATE 7.00%

INGREDIENTS

WATER (AQUA PURIFICATA) PURIFIED, CYCLOPENTASILOXANE, BUTYLENE GLYCOL, SILICA, DIMETHICONE, PHENYL TRIMETHICONE, BIS-PEG/PPG-14/14 DIMETHICONE, MAGNESIUM SULFATE, TRIMETHYLSILOXYSILICATE, TITANIUM DIOXIDE, TOCOPHERYL ACETATE, RETINYL PALMITATE, ASCORBYL PALMITATE, DISTEARDIMONIUM HECTORITE, TRIETHOXYCAPRYLYLSILANE, POLYGLYCERYL-4 ISOSTEARATE, HEXYL LAURATE, CETYL PEG/PPG-10/1 DIMETHICONE, LAURETH-7, TRIETHYL CITRATE, PHENOXYETHANOL, METHYLPARABEN [+/-(MAY CONTAIN): MICA, TITANIUM DIOXIDE (CI 77891), IRON OXIDES (CI 77491, CI 77492, CI 77499), BISMUTH OXYCHLORIDE (CI 77163), CHROMIUM OXIDE GREENS (CI 77288)] <ILN28730>

DIST. BY/PAR: MAKE-UP ART COSMETICS
TORONTO, ONTARIO, CANADA M5V 1R7,
LONDON W1K 3BQ. / M49W

PRINCIPAL DISPLAY PANEL - 30 ML Bottle Carton

M•A•C

HYPER REAL SPF 15
FOUNDATION

30 ML/1.0 US FL OZ e